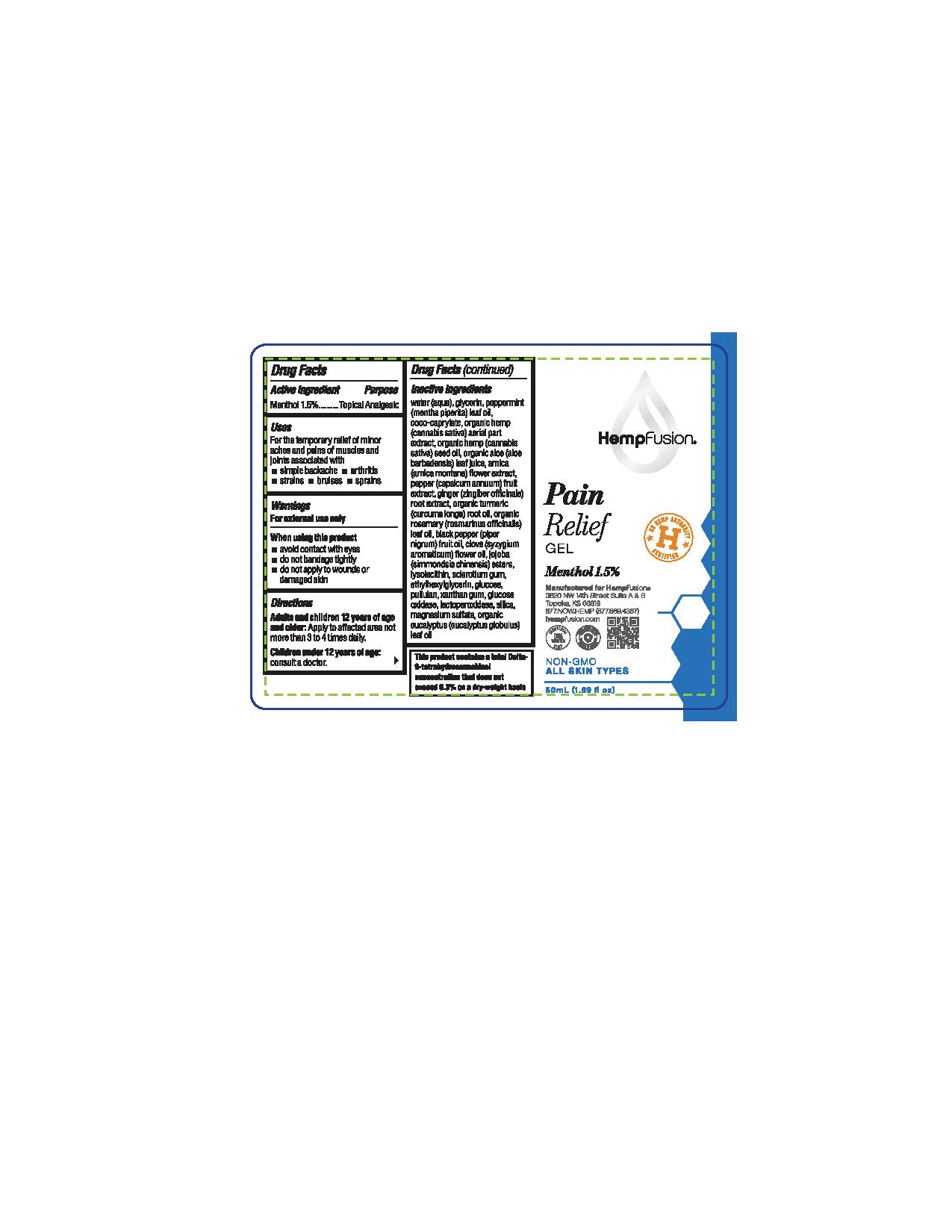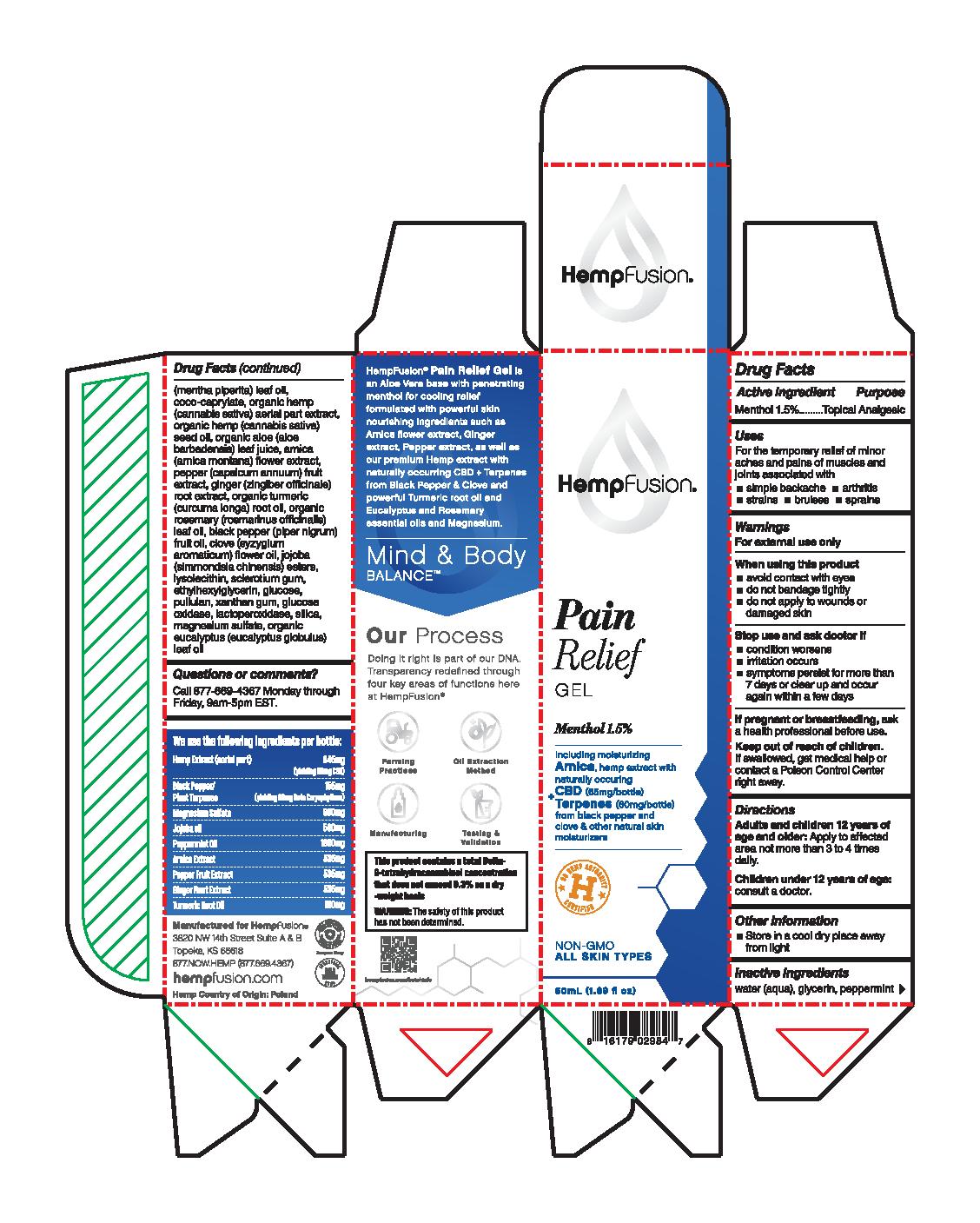 DRUG LABEL: Pain Relief Gel
NDC: 73672-989 | Form: GEL
Manufacturer: HEMPFUSION, INC.
Category: otc | Type: HUMAN OTC DRUG LABEL
Date: 20210317

ACTIVE INGREDIENTS: MENTHOL 15 mg/1 mL
INACTIVE INGREDIENTS: CANNABIS SATIVA SEED OIL; ARNICA MONTANA FLOWER; HEMP; PEPPERMINT OIL; ALOE; ROSEMARY OIL; CLOVE OIL; HYDROLYZED JOJOBA ESTERS (ACID FORM); WATER; CAPSICUM; GINGER; TURMERIC OIL; MYELOPEROXIDASE; SILICON DIOXIDE; BLACK PEPPER OIL; BETASIZOFIRAN; ETHYLHEXYLGLYCERIN; ANHYDROUS DEXTROSE; PULLULAN; XANTHAN GUM; GLUCOSE OXIDASE; EUCALYPTUS OIL; COCO-CAPRYLATE; LYSOPHOSPHATIDYLCHOLINE, SOYBEAN; MAGNESIUM SULFATE, UNSPECIFIED FORM

Pain Relief Gel

Active Ingredients

Menthol 1.5%

Purpose

Menthol 1.5%........Topical Analgesic

Uses

For the temporary relief of minor aches and pains of muscles and joints associated with

- simple backache
- arthritis
- strains
- bruises
- sprains

Warnings

For external use only

When using this product

- avoid contact with eyes
- do not bandage tightly
- do not apply to wounds or damaged skin

Stop use and ask doctor if

- condition worsens
- irritation occurs
- symptoms persist for more than 7 days or clear up and occur again within a few days

PREGNANCY OR BREAST FEEDING

If pregnant or breastfeeding, ask a health professional before use.

Keep out of reach of children. If swallowed, get medical help or contact a Poison Control Center right away.

Directions

Adults and children 12 years of age and older: Apply to affected area not more than 3 to 4 times daily.

Children under 12 years of age: consult a doctor.

Other information

- Store in a cool dry place away from light

Inactive ingredients

water (aqua), glycerin, peppermint (mentha piperita) leaf oil, coco-caprylate, organic hemp (cannabis sativa) aerial part extract, organic hemp (cannabis sativa) seed oil, organic aloe (aloe barbadensis) leaf juice, arnica (arnica montana) flower extract, pepper (capsicum annuum) fruit extract, ginger (zingiber officinale) root extract, organic turmeric (curcuma longa) root oil, organic rosemary (rosmarinus officinalis) leaf oil, black pepper (piper nigrum) fruit oil, clove (syzgium aromaticum) flower oil, jojoba (simmondsia chinensis) esters, lysolecithin, sclerotium gum, ethylhexylglycerin, glucose, pullulan, xanthan gum, glucose oxidase, lactoperoxidase, silica, magnesium sulfate, organic eucalyptus (eucalyptus globulus) leaf oil

Questions or comments?

Call 877-669-4367 Monday through Friday, 9am-5pm EST.

PACKAGE LABEL

HempFusion

Pain Relief Gel

Menthol 1.5%

Including moisturizing Arnica, hemp extract with naturally occuring CBD (65mg/bottle) + Terpenes (60mg/bottle) from black pepper and clove & other natural skin moisturizers

U.S. HEMP AUTHORITY CERTIFIED

NON-GMO

ALL SKIN TYPES

50mL (1.69 fl oz)